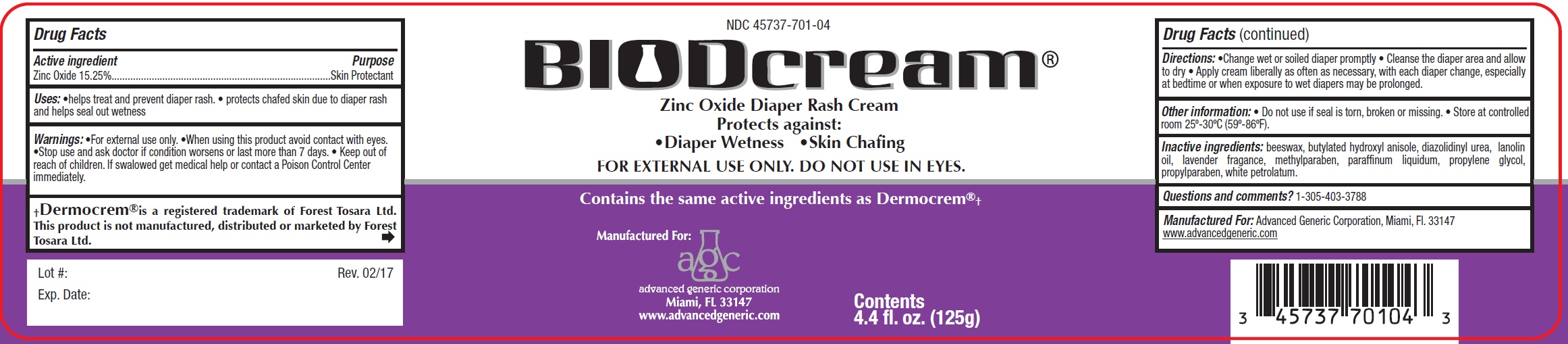 DRUG LABEL: BioDCream
NDC: 45737-701 | Form: CREAM
Manufacturer: Advanced Generic Corporation
Category: otc | Type: HUMAN OTC DRUG LABEL
Date: 20241220

ACTIVE INGREDIENTS: ZINC OXIDE 15.25 g/100 g
INACTIVE INGREDIENTS: YELLOW WAX; MINERAL OIL; BUTYLATED HYDROXYANISOLE; PROPYLENE GLYCOL; DIAZOLIDINYL UREA; METHYLPARABEN; PROPYLPARABEN; LANOLIN OIL; PETROLATUM

AGC-BioDCream 701

Active Ingredient

Zinc Oxide 15.25%

Purpose

Skin protectant

Uses

- helps treat and prevent diaper rash
- protects chafed skin due to diaper rash and helps seal out wetness

Warnings

For external use only.

- When using this product avoid contact with eyes.
- Stop use and ask doctor if condition worsens or lasts more than 7 days

Keep out of reach of children. If swallowed get medical help or contact a Poison Control Center immediately.

Directions

- Change wet or soiled diaper promptly
- Cleanse the diaper area and allow to dry
- Apply Cream liberally as often as necessary, with each diaper change, especially at bedtime or when exposure to wet diapers may be prolonged.

Inactive ingredients

beeswax, butylated hydroxyl anisole, diazolidinyl urea, lanolin oil, lavender fragrance, methylparaben, paraffinum liquidum, propylene glycol, propylparaben, white petrolatum.

Questions or comments:

1-305-403-3788